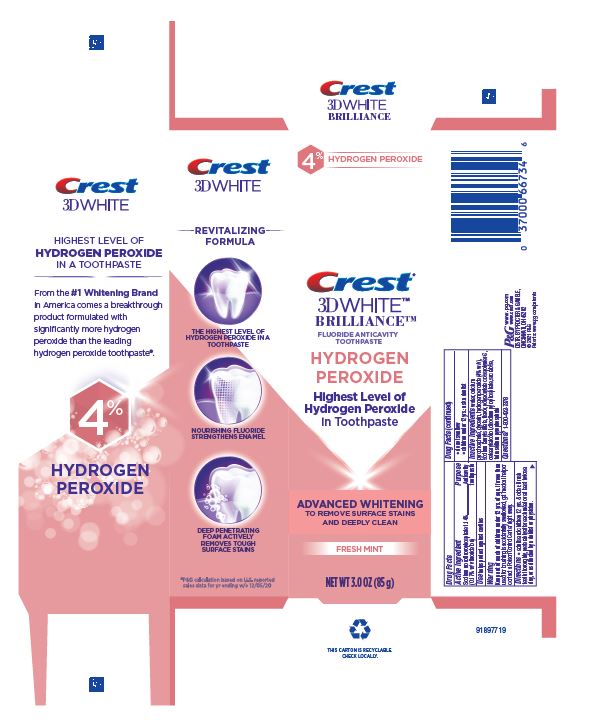 DRUG LABEL: Crest 3D White Brilliance
NDC: 69423-959 | Form: PASTE, DENTIFRICE
Manufacturer: The Procter & Gamble Manufacturing Company
Category: otc | Type: HUMAN OTC DRUG LABEL
Date: 20260106

ACTIVE INGREDIENTS: SODIUM MONOFLUOROPHOSPHATE 1.7 mg/1 g
INACTIVE INGREDIENTS: CALCIUM PYROPHOSPHATE; GLYCERIN; HYDROGEN PEROXIDE; AMMONIUM ACRYLOYLDIMETHYLTAURATE, DIMETHYLACRYLAMIDE, LAURYL METHACRYLATE AND LAURETH-4 METHACRYLATE COPOLYMER, TRIMETHYLOLPROPANE TRIACRYLATE CROSSLINKED (45000 MPA.S); SODIUM PYROPHOSPHATE; SODIUM LAURYL SULFATE; CETOSTEARYL ALCOHOL; SODIUM ACID PYROPHOSPHATE; WATER; SUCRALOSE

Crest 3D White Brilliance Advanced Whitening Fresh Mint

Drug Facts

Sodium monofluorophosphate 1.14%

(0.17% w/v fluoride ion)

Purpose

Anticavity toothpaste

Use

helps protect against cavities

Warning

Keep out of reach of children under 12 yrs. of age. If more than used for brushing is accidentally swallowed, get medical help or contact a Poison Control Center right away.

Directions

- adults and children 12 yrs. & older: Brush teeth thoroughly, preferably after each meal or at least twice a day, or as directed by a dentist or physician.
- do not swallow
- children under 12 yrs.: ask a dentist

Inactive ingredients

water, calcium pyrophosphate, glycerin, hydrogen peroxide (4% w/v), sodium lauryl sulfate, flavor, polyacrylate crosspolymer-6, cetearyl alcohol, disodium pyrophosphate, sucralose, tetrasodium pyrophosphate

Questions?

1-800-492-7378

DISTR. BY PROCTER & GAMBLE, CINCINNATI, OH 45202

85g tube in carton

4% HYDROGEN PEROXIDE

Crest®

3DWHITE™

BRILLIANCE™

FLUORIDE ANTICAVITY TOOTHPASTE

HYDROGEN PEROXIDE

Highest Level of Hydrogen Peroxide in Toothpaste

ADVANCED WHITENING TO REMOVE SURFACE STAINS AND DEEPLY CLEAN

FRESH MINT

NET WT 3.0 OZ (85 g)